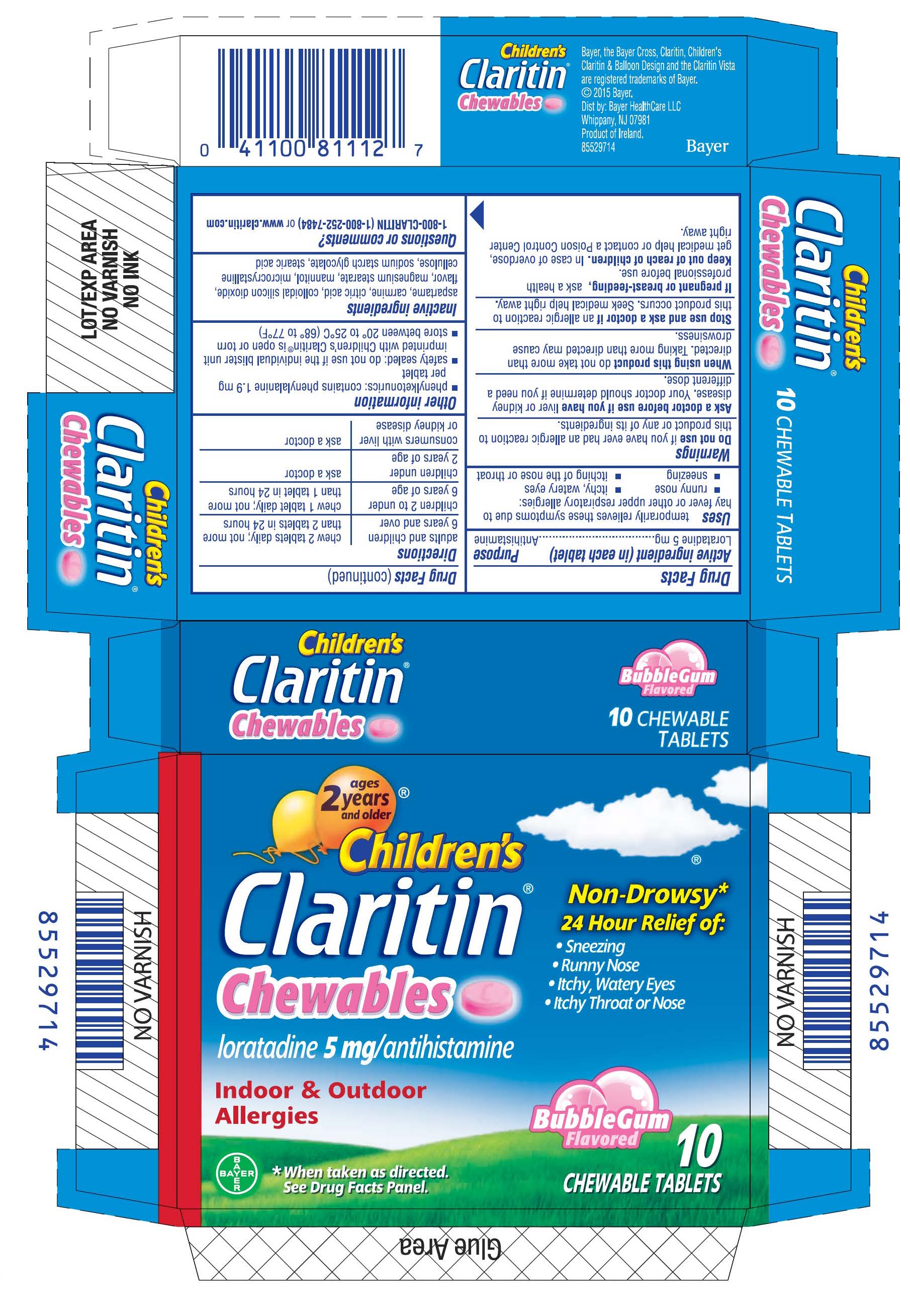 DRUG LABEL: Claritin
NDC: 11523-4330 | Form: TABLET, CHEWABLE
Manufacturer: Bayer HealthCare LLC.
Category: otc | Type: HUMAN OTC DRUG LABEL
Date: 20251205

ACTIVE INGREDIENTS: LORATADINE 5 mg/1 1
INACTIVE INGREDIENTS: SILICON DIOXIDE; MAGNESIUM STEARATE; MANNITOL; CELLULOSE, MICROCRYSTALLINE; STEARIC ACID; ASPARTAME

Children's Claritin Chewable

Active Ingredients

Loratadine 5 mg

Purpose

Antihistamine

INDICATIONS AND USAGE

temporarily relieves these symptoms due to hay fever or other upper respiratory allergies:

- runny nose
- sneezing
- itchy, watery eyes
- itching of the nose or throat

Do not use if you have ever had an allergic reaction to this product or any of its ingredients.

AS a doctor before use if you have

Ask a doctor before use if you have liver or kidney disease. Your doctor should determine if you need a different dose.

When using this product do not take more than directed. Taking more than directed may cause drowsiness.

Stop use and ask a doctor if an allergic reaction to this product occurs. Seek medical help right away.

PREGNANCY OR BREAST FEEDING

If pregnant or breast-feeding, ask a health professional before use.

Keep out of reach of children. In case of overdose, get medical help or contact a Poison Control Center right away.

Directions

adults and children 6 years and over | chew 2 tablets daily; not more than 2 tablets in 24 hours
children 2 to under 6 years of age | chew 1 tablet daily; not more than 1 tablet in 24 hours
children under 2 years of age | ask a doctor
consumers with liver or kidney disease | ask a doctor

Other information

- phenylketonurics: contains phenylalanine 1.9 mg per tablet
- safety sealed: do not use if the individual blister unit imprinted with Children’s Claritin® is open or torn
- store between 20° to 25°C (68° to 77°F)

INACTIVE INGREDIENT

aspartame, carmine, citric acid, colloidal silicon dioxide, flavor, magnesium stearate, mannitol, microcrystalline cellulose, sodium starch glycolate, stearic acid

QUESTIONS

1-800-CLARITIN

PACKAGE LABEL

ages

2 years®

and older

Children's

Claritin®

Chewables

loratadine 5 mg/antihistamine

Indoor & Outdoor

Allergies

*When taken as directed.

See Drug Facts Panel

Non-Drowsy*

24 Hour Relief of:

- Sneezing
- Runny Nose
- Itchy, Watery Eyes
- Itchy Throat or Nose

Bubblegum

Flavored

10

Chewable Tablets